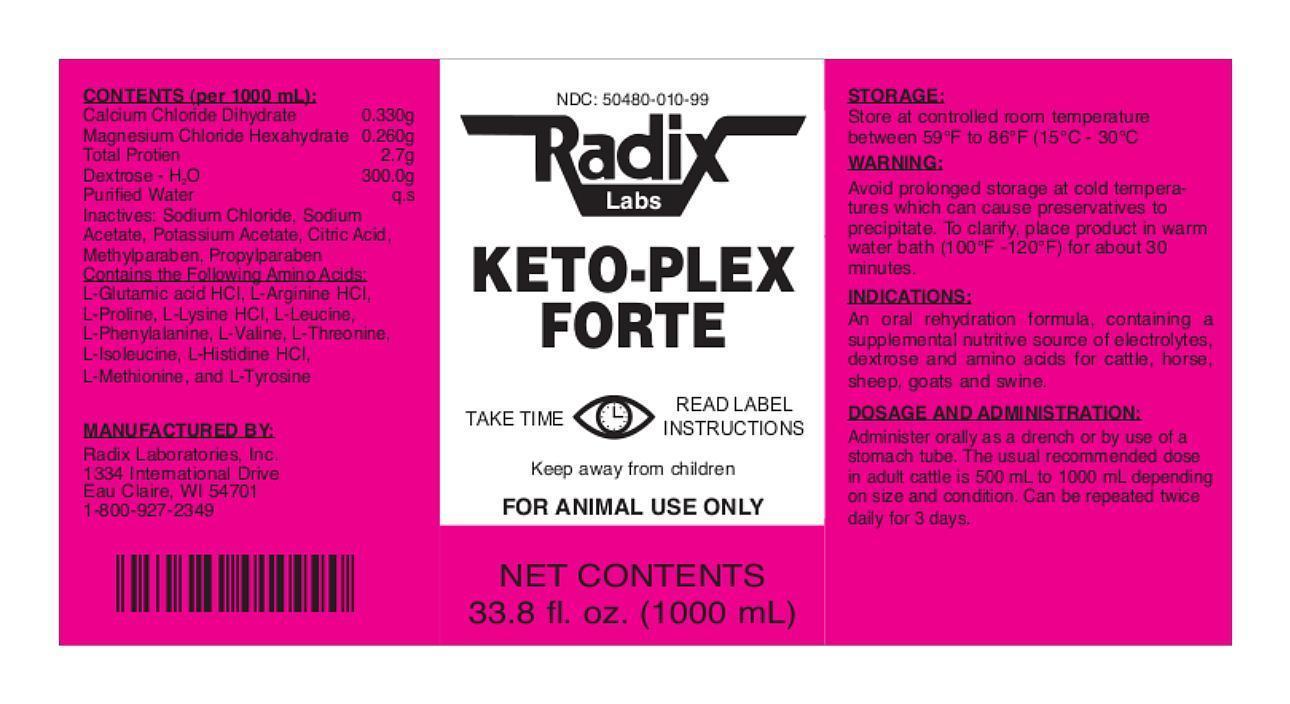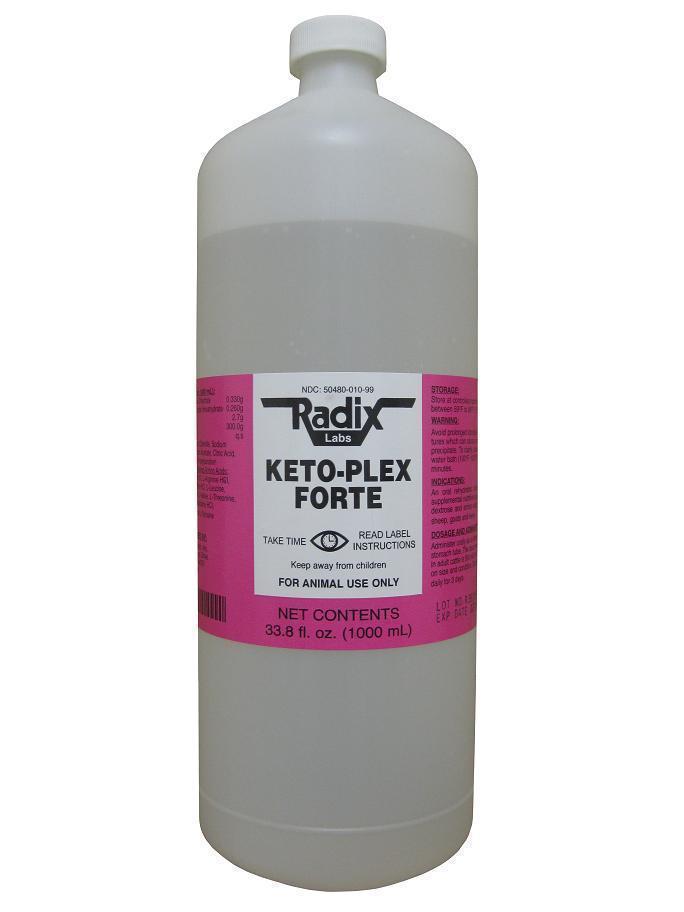 DRUG LABEL: Keto-Plex Forte
NDC: 50480-010 | Form: LIQUID
Manufacturer: Radix Laboratories, Inc.
Category: animal | Type: OTC ANIMAL DRUG LABEL
Date: 20141222

ACTIVE INGREDIENTS: CALCIUM CHLORIDE 0.330 g/1000 mL; MAGNESIUM CHLORIDE 0.260 g/1000 mL; AMINO ACIDS 2.7 g/1000 mL; DEXTROSE MONOHYDRATE 300 g/1000 mL

KETO-PLEX FORTE

CONTENTS (Per 1000ml):

- Calcium Chloride Dihydrate ..................0.330g
- Magnesium Chloride Hexahydrate .......0.260g
- Total Protien ............................................2.7g
- Dextrose H2O ......................................300.0g
- Purified Water ..........................................q.s.

Inactives:

- Sodium Chloride, Sodium
  Acetate, Potassium Acetate, Citric Acid,
  Methylparaben, Propylparaben
- Contains the Following Amino Acids:
  L-Glutamic acid HCI, L-Arginine HCI,
  L-Proline, L-Lysine HCI, L-Leucine,
  L-Phenylalanine, L-Valine, L-Threonine,
  L-Isoleucine, L-Histidine HCI,
  L-Methionine, and L-Tyrosine

Indications:

- An oral rehydration formula, containing a
  supplemental nutritive source of electrolytes,
  dextrose and amino acids for cattle, horse,
  sheep, goats and swine.

Storage:

- Store at controlled room temperature between 59oF to 86oF (15oC -30oC).

Warnings:

- Avoid storage at cold temperatures which can cause product to become cloudy.
- To clarify place product in warm water bath (100oF-120oF) for about 30 minutes.

Dosage and administration:

- Administer orally as a drench or by use of a stomach tube.
- The usual recommended dose in adult cattle is 500mL to 1000mL depending on size and condition.
- Can be repeated twice daily for 3 days.

Keep Away From Children

- For animal use only.